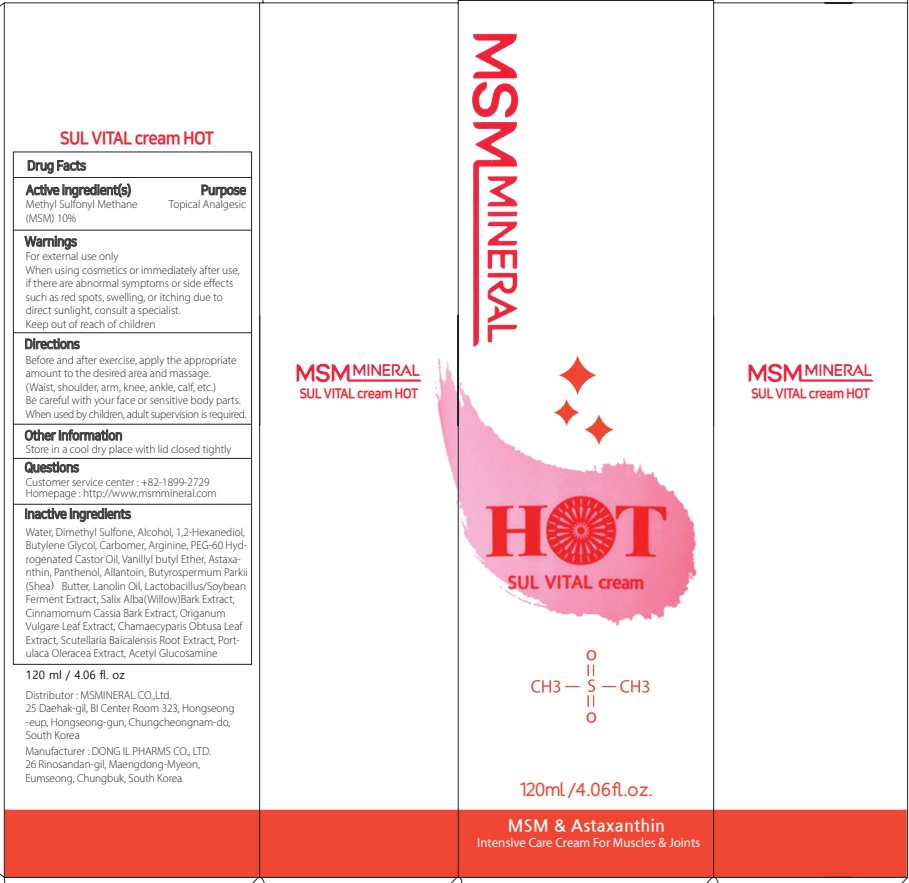 DRUG LABEL: SUL VITAL HOT
NDC: 82409-030 | Form: CREAM
Manufacturer: MSMINERAL CO.,Ltd.
Category: otc | Type: HUMAN OTC DRUG LABEL
Date: 20250115

ACTIVE INGREDIENTS: DIMETHYL SULFONE 10 g/100 mL
INACTIVE INGREDIENTS: WATER; BUTYLENE GLYCOL; ALCOHOL

ACTIVE INGREDIENT

Methyl Sulfonyl Methane(MSM) 10%

INACTIVE INGREDIENTS

Water, Dimethyl Sulfone, Alcohol, 1,2-Hexanediol, Butylene Glycol, Carbomer, Arginine, PEG-60 Hydrogenated Castor Oil, Vanillyl butyl Ether, Astaxanthin, Panthenol, Allantoin, Butyrospermum Parkii (Shea）Butter, Lanolin Oil, Lactobacillus/Soybean Ferment Extract, Salix Alba （Willow） Bark Extract, Cinnamomum Cassia Bark Extract, Origanum Vulgare Leaf Extract, Chamaecyparis Obtusa Leaf Extract, Scutellaria Baicalensis Root Extract, Portulaca Oleracea Extract, Acetyl Glucosamine

PURPOSE

Topical Analgesic

Uses

■ Provides support for joint and cartilage health.

WARNINGS

■ For external use only
■ When using cosmetics or immediately after use, if there are abnormal symptoms or side effects such as red spots, swelling, or itching due to direct sunlight, consult a specialist.
■ Keep out of reach of children

KEEP OUT OF REACH OF CHILDREN

Directions

■ Before and after exercise, apply the appropriate amount to the desired area and massage.

(Waist, shoulder, arm, knee, ankle, calf, etc.) Be careful with your face or sensitive body parts.When used by children, adult supervision is required.

Other Information

■ Store in a cool dry place with lid closed tightly

Questions

■ Customer service center : 1-770-878-3322
■ Homepage : http://www.msmmineral.com